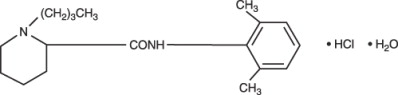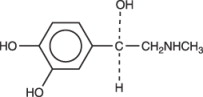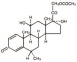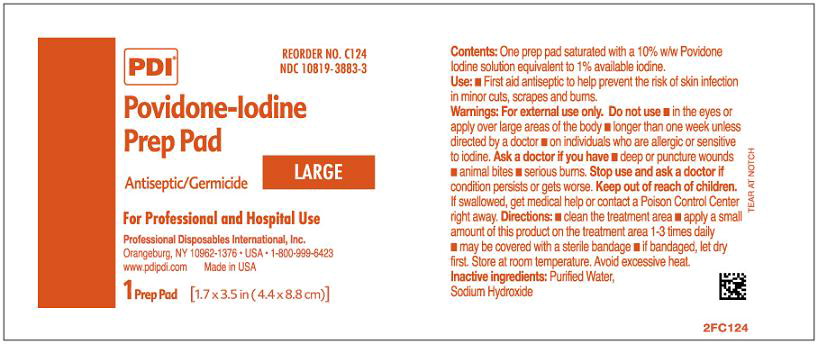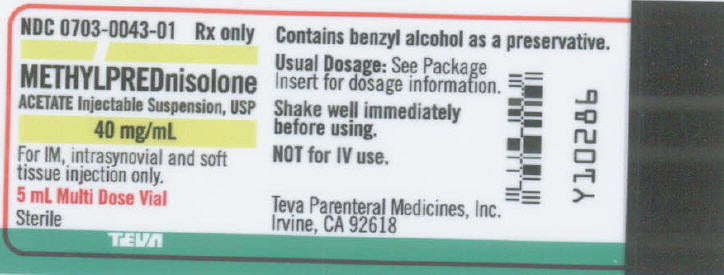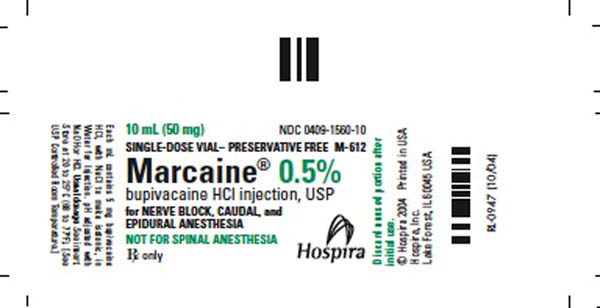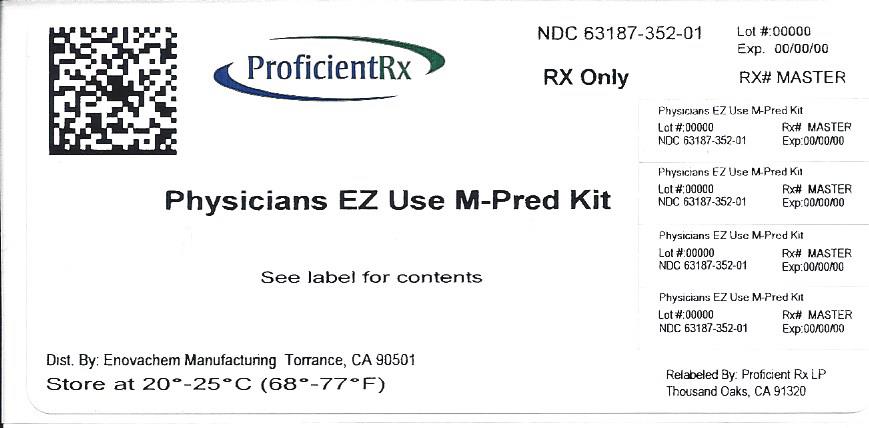 DRUG LABEL: Physicians EZ Use M-pred
NDC: 63187-352 | Form: KIT | Route: INTRAMUSCULAR
Manufacturer: Proficient Rx LP
Category: prescription | Type: HUMAN PRESCRIPTION DRUG LABEL
Date: 20130530

ACTIVE INGREDIENTS: METHYLPREDNISOLONE ACETATE 40 mg/1 mL; BUPIVACAINE HYDROCHLORIDE 5 mg/1 mL; POVIDONE-IODINE 10 mg/1 g
INACTIVE INGREDIENTS: POLYETHYLENE GLYCOL 3350 29.1 mg/1 mL; POLYSORBATE 80 1.94 mg/1 mL; SODIUM PHOSPHATE, MONOBASIC 6.8 mg/1 mL; SODIUM PHOSPHATE, DIBASIC 1.42 mg/1 mL; BENZYL ALCOHOL 9.16 mg/1 mL; SODIUM CHLORIDE; SODIUM HYDROXIDE; HYDROCHLORIC ACID; SODIUM CHLORIDE; SODIUM HYDROXIDE; HYDROCHLORIC ACID; WATER; WATER; SODIUM HYDROXIDE

Marcaine™

Bupivacaine Hydrochloride Injection, USP

Marcaine™

With Epinephrine 1:200,000 (as bitartrate)

Bupivacaine Hydrochloride and Epinephrine Injection, USP Rx only

DESCRIPTION

Bupivacaine hydrochloride is 2-Piperidinecarboxamide, 1-butyl-N-(2,6-dimethylphenyl)-, monohydrochloride, monohydrate, a white crystalline powder that is freely soluble in 95 percent ethanol, soluble in water, and slightly soluble in chloroform or acetone. It has the following structural formula:

Epinephrine is (-)-3,4-Dihydroxy-α-[(methylamino)methyl] benzyl alcohol. It has the following structural formula:

MARCAINE is available in sterile isotonic solutions with and without epinephrine (as bitartrate) 1:200,000 for injection via local infiltration, peripheral nerve block, and caudal and lumbar epidural blocks. Solutions of MARCAINE may be autoclaved if they do not contain epinephrine. Solutions are clear and colorless.

Bupivacaine is related chemically and pharmacologically to the aminoacyl local anesthetics. It is a homologue of mepivacaine and is chemically related to lidocaine. All three of these anesthetics contain an amide linkage between the aromatic nucleus and the amino, or piperidine group. They differ in this respect from the procaine-type local anesthetics, which have an ester linkage.

MARCAINE — Sterile isotonic solutions containing sodium chloride. In multiple-dose vials, each mL also contains 1 mg methylparaben as antiseptic preservative. The pH of these solutions is adjusted to between 4 and 6.5 with sodium hydroxide or hydrochloric acid.

MARCAINE with epinephrine 1:200,000 (as bitartrate)—Sterile isotonic solutions containing sodium chloride. Each mL contains bupivacaine hydrochloride and 0.0091 mg epinephrine bitartrate, with 0.5 mg sodium metabisulfite, 0.001 mL monothioglycerol, and 2 mg ascorbic acid as antioxidants, 0.0017 mL 60% sodium lactate buffer, and 0.1 mg edetate calcium disodium as stabilizer. In multiple-dose vials, each mL also contains 1 mg methylparaben as antiseptic preservative. The pH of these solutions is adjusted to between 3.4 and 4.5 with sodium hydroxide or hydrochloric acid. The specific gravity of MARCAINE 0.5% with epinephrine 1:200,000 (as bitartrate) at 25°C is 1.008 and at 37°C is 1.008.

CLINICAL PHARMACOLOGY

Local anesthetics block the generation and the conduction of nerve impulses, presumably by increasing the threshold for electrical excitation in the nerve, by slowing the propagation of the nerve impulse, and by reducing the rate of rise of the action potential. In general, the progression of anesthesia is related to the diameter, myelination, and conduction velocity of affected nerve fibers. Clinically, the order of loss of nerve function is as follows: (1) pain, (2) temperature, (3) touch, (4) proprioception, and (5) skeletal muscle tone.

Systemic absorption of local anesthetics produces effects on the cardiovascular and central nervous systems (CNS). At blood concentrations achieved with normal therapeutic doses, changes in cardiac conduction, excitability, refractoriness, contractility, and peripheral vascular resistance are minimal. However, toxic blood concentrations depress cardiac conduction and excitability, which may lead to atrioventricular block, ventricular arrhythmias, and cardiac arrest, sometimes resulting in fatalities. In addition, myocardial contractility is depressed and peripheral vasodilation occurs, leading to decreased cardiac output and arterial blood pressure. Recent clinical reports and animal research suggest that these cardiovascular changes are more likely to occur after unintended intravascular injection of bupivacaine. Therefore, incremental dosing is necessary.

Following systemic absorption, local anesthetics can produce central nervous system stimulation, depression, or both. Apparent central stimulation is manifested as restlessness, tremors and shivering progressing to convulsions, followed by depression and coma progressing ultimately to respiratory arrest. However, the local anesthetics have a primary depressant effect on the medulla and on higher centers. The depressed stage may occur without a prior excited state.

Pharmacokinetics: The rate of systemic absorption of local anesthetics is dependent upon the total dose and concentration of drug administered, the route of administration, the vascularity of the administration site, and the presence or absence of epinephrine in the anesthetic solution. A dilute concentration of epinephrine (1:200,000 or 5 mcg/mL) usually reduces the rate of absorption and peak plasma concentration of MARCAINE, permitting the use of moderately larger total doses and sometimes prolonging the duration of action.

The onset of action with MARCAINE is rapid and anesthesia is long lasting. The duration of anesthesia is significantly longer with MARCAINE than with any other commonly used local anesthetic. It has also been noted that there is a period of analgesia that persists after the return of sensation, during which time the need for strong analgesics is reduced.

The onset of action following dental injections is usually 2 to 10 minutes and anesthesia may last two or three times longer than lidocaine and mepivacaine for dental use, in many patients up to 7 hours. The duration of anesthetic effect is prolonged by the addition of epinephrine 1:200,000.

Local anesthetics are bound to plasma proteins in varying degrees. Generally, the lower the plasma concentration of drug the higher the percentage of drug bound to plasma proteins.

Local anesthetics appear to cross the placenta by passive diffusion. The rate and degree of diffusion is governed by (1) the degree of plasma protein binding, (2) the degree of ionization, and (3) the degree of lipid solubility. Fetal/ maternal ratios of local anesthetics appear to be inversely related to the degree of plasma protein binding, because only the free, unbound drug is available for placental transfer. MARCAINE with a high protein binding capacity (95%) has a low fetal/maternal ratio (0.2 to 0.4). The extent of placental transfer is also determined by the degree of ionization and lipid solubility of the drug. Lipid soluble, nonionized drugs readily enter the fetal blood from the maternal circulation.

Depending upon the route of administration, local anesthetics are distributed to some extent to all body tissues, with high concentrations found in highly perfused organs such as the liver, lungs, heart, and brain.

Pharmacokinetic studies on the plasma profile of MARCAINE after direct intravenous injection suggest a three-compartment open model. The first compartment is represented by the rapid intravascular distribution of the drug. The second compartment represents the equilibration of the drug throughout the highly perfused organs such as the brain, myocardium, lungs, kidneys, and liver. The third compartment represents an equilibration of the drug with poorly perfused tissues, such as muscle and fat. The elimination of drug from tissue distribution depends largely upon the ability of binding sites in the circulation to carry it to the liver where it is metabolized.

After injection of MARCAINE for caudal, epidural, or peripheral nerve block in man, peak levels of bupivacaine in the blood are reached in 30 to 45 minutes, followed by a decline to insignificant levels during the next three to six hours.

Various pharmacokinetic parameters of the local anesthetics can be significantly altered by the presence of hepatic or renal disease, addition of epinephrine, factors affecting urinary pH, renal blood flow, the route of drug administration, and the age of the patient. The half-life of MARCAINE in adults is 2.7 hours and in neonates 8.1 hours.

In clinical studies, elderly patients reached the maximal spread of analgesia and maximal motor blockade more rapidly than younger patients. Elderly patients also exhibited higher peak plasma concentrations following administration of this product. The total plasma clearance was decreased in these patients.

Amide-type local anesthetics such as MARCAINE are metabolized primarily in the liver via conjugation with glucuronic acid. Patients with hepatic disease, especially those with severe hepatic disease, may be more susceptible to the potential toxicities of the amide-type local anesthetics. Pipecoloxylidine is the major metabolite of MARCAINE.

The kidney is the main excretory organ for most local anesthetics and their metabolites. Urinary excretion is affected by urinary perfusion and factors affecting urinary pH. Only 6% of bupivacaine is excreted unchanged in the urine.

When administered in recommended doses and concentrations, MARCAINE does not ordinarily produce irritation or tissue damage and does not cause methemoglobinemia.

INDICATIONS AND USAGE

MARCAINE is indicated for the production of local or regional anesthesia or analgesia for surgery, dental and oral surgery procedures, diagnostic and therapeutic procedures, and for obstetrical procedures. Only the 0.25% and 0.5% concentrations are indicated for obstetrical anesthesia. (See WARNINGS.)

Experience with nonobstetrical surgical procedures in pregnant patients is not sufficient to recommend use of 0.75% concentration of MARCAINE in these patients.

MARCAINE is not recommended for intravenous regional anesthesia (Bier Block). See WARNINGS.

The routes of administration and indicated MARCAINE concentrations are:

∙ local infiltration 0.25%

∙ peripheral nerve block 0.25% and 0.5%

∙ retrobulbar block 0.75%

∙ sympathetic block 0.25%

∙ lumbar epidural 0.25%, 0.5%, and 0.75%

(0.75% not for obstetrical anesthesia)

∙ caudal 0.25% and 0.5%

∙ epidural test dose 0.5% with epinephrine 1:200,000

∙ dental blocks 0.5% with epinephrine 1:200,000

(See DOSAGE AND ADMINISTRATION for additional information.)

Standard textbooks should be consulted to determine the accepted procedures and techniques for the administration of MARCAINE.

CONTRAINDICATIONS

MARCAINE is contraindicated in obstetrical paracervical block anesthesia. Its use in this technique has resulted in fetal bradycardia and death.

MARCAINE is contraindicated in patients with a known hypersensitivity to it or to any local anesthetic agent of the amide-type or to other components of MARCAINE solutions.

WARNINGS

THE 0.75% CONCENTRATION OF MARCAINE IS NOT RECOMMENDED FOR OBSTETRICAL ANESTHESIA. THERE HAVE BEEN REPORTS OF CARDIAC ARREST WITH DIFFICULT RESUSCITATION OR DEATH DURING USE OF MARCAINE FOR EPIDURAL ANESTHESIA IN OBSTETRICAL PATIENTS. IN MOST CASES, THIS HAS FOLLOWED USE OF THE 0.75% CONCENTRATION. RESUSCITATION HAS BEEN DIFFICULT OR IMPOSSIBLE DESPITE APPARENTLY ADEQUATE PREPARATION AND APPROPRIATE MANAGEMENT. CARDIAC ARREST HAS OCCURRED AFTER CONVULSIONS RESULTING FROM SYSTEMIC TOXICITY, PRESUMABLY FOLLOWING UNINTENTIONAL INTRAVASCULAR INJECTION. THE 0.75% CONCENTRATION SHOULD BE RESERVED FOR SURGICAL PROCEDURES WHERE A HIGH DEGREE OF MUSCLE RELAXATION AND PROLONGED EFFECT ARE NECESSARY.

LOCAL ANESTHETICS SHOULD ONLY BE EMPLOYED BY CLINICIANS WHO ARE WELL VERSED IN DIAGNOSIS AND MANAGEMENT OF DOSE-RELATED TOXICITY AND OTHER ACUTE EMERGENCIES WHICH MIGHT ARISE FROM THE BLOCK TO BE EMPLOYED, AND THEN ONLY AFTER INSURING THE IMMEDIATE AVAILABILITY OF OXYGEN, OTHER RESUSCITATIVE DRUGS, CARDIOPULMONARY RESUSCITATIVE EQUIPMENT, AND THE PERSONNEL RESOURCES NEEDED FOR PROPER MANAGEMENT OF TOXIC REACTIONS AND RELATED EMERGENCIES. (See also ADVERSE REACTIONS, PRECAUTIONS, and OVERDOSAGE.) DELAY IN PROPER MANAGEMENT OF DOSE-RELATED TOXICITY, UNDERVENTILATION FROM ANY CAUSE, AND/OR ALTERED SENSITIVITY MAY LEAD TO THE DEVELOPMENT OF ACIDOSIS, CARDIAC ARREST AND, POSSIBLY, DEATH.

Local anesthetic solutions containing antimicrobial preservatives, i.e., those supplied in multiple-dose vials, should not be used for epidural or caudal anesthesia because safety has not been established with regard to intrathecal injection, either intentionally or unintentionally, of such preservatives.

Intra-articular infusions of local anesthetics following arthroscopic and other surgical procedures is an unapproved use, and there have been post-marketing reports of chondrolysis in patients receiving such infusions. The majority of reported cases of chondrolysis have involved the shoulder joint; cases of gleno-humeral chondrolysis have been described in pediatric and adult patients following intra-articular infusions of local anesthetics with and without epinephrine for periods of 48 to 72 hours. There is insufficient information to determine whether shorter infusion periods are not associated with these findings. The time of onset of symptoms, such as joint pain, stiffness and loss of motion can be variable, but may begin as early as the 2nd month after surgery. Currently, there is no effective treatment for chondrolysis; patients who experienced chondrolysis have required additional diagnostic and therapeutic procedures and some required arthroplasty or shoulder replacement.

It is essential that aspiration for blood or cerebrospinal fluid (where applicable) be done prior to injecting any local anesthetic, both the original dose and all subsequent doses, to avoid intravascular or subarachnoid injection. However, a negative aspiration does not ensure against an intravascular or subarachnoid injection.

MARCAINE with epinephrine 1:200,000 or other vasopressors should not be used concomitantly with ergot-type oxytocic drugs, because a severe persistent hypertension may occur. Likewise, solutions of MARCAINE containing a vasoconstrictor, such as epinephrine, should be used with extreme caution in patients receiving monoamineoxidase inhibitors (MAOI) or antidepressants of the triptyline or imipramine types, because severe prolonged hypertension may result.

Until further experience is gained in pediatric patients younger than 12 years, administration of MARCAINE in this age group is not recommended.

Mixing or the prior or intercurrent use of any other local anesthetic with MARCAINE cannot be recommended because of insufficient data on the clinical use of such mixtures.

There have been reports of cardiac arrest and death during the use of MARCAINE for intravenous regional anesthesia (Bier Block). Information on safe dosages and techniques of administration of MARCAINE in this procedure is lacking. Therefore, MARCAINE is not recommended for use in this technique.

MARCAINE with epinephrine 1:200,000 contains sodium metabisulfite, a sulfite that may cause allergic-type reactions including anaphylactic symptoms and life-threatening or less severe asthmatic episodes in certain susceptible people. The overall prevalence of sulfite sensitivity in the general population is unknown and probably low. Sulfite sensitivity is seen more frequently in asthmatic than in nonasthmatic people. Single-dose ampuls and single-dose vials of MARCAINE without epinephrine do not contain sodium metabisulfite.

PRECAUTIONS

GENERAL PRECAUTIONS

General: The safety and effectiveness of local anesthetics depend on proper dosage, correct technique, adequate precautions, and readiness for emergencies. Resuscitative equipment, oxygen, and other resuscitative drugs should be available for immediate use. (See WARNINGS, ADVERSE REACTIONS, and OVERDOSAGE.) During major regional nerve blocks, the patient should have IV fluids running via an indwelling catheter to assure a functioning intravenous pathway. The lowest dosage of local anesthetic that results in effective anesthesia should be used to avoid high plasma levels and serious adverse effects. The rapid injection of a large volume of local anesthetic solution should be avoided and fractional (incremental) doses should be used when feasible.

Epidural Anesthesia: During epidural administration of MARCAINE, 0.5% and 0.75% solutions should be administered in incremental doses of 3 mL to 5 mL with sufficient time between doses to detect toxic manifestations of unintentional intravascular or intrathecal injection. Injections should be made slowly, with frequent aspirations before and during the injection to avoid intravascular injection. Syringe aspirations should also be performed before and during each supplemental injection in continuous (intermittent) catheter techniques. An intravascular injection is still possible even if aspirations for blood are negative.

During the administration of epidural anesthesia, it is recommended that a test dose be administered initially and the effects monitored before the full dose is given. When using a “continuous” catheter technique, test doses should be given prior to both the original and all reinforcing doses, because plastic tubing in the epidural space can migrate into a blood vessel or through the dura. When clinical conditions permit, the test dose should contain epinephrine (10 mcg to 15 mcg has been suggested) to serve as a warning of unintended intravascular injection. If injected into a blood vessel, this amount of epinephrine is likely to produce a transient “epinephrine response” within 45 seconds, consisting of an increase in heart rate and/or systolic blood pressure, circumoral pallor, palpitations, and nervousness in the unsedated patient. The sedated patient may exhibit only a pulse rate increase of 20 or more beats per minute for 15 or more seconds. Therefore, following the test dose, the heart rate should be monitored for a heart rate increase. Patients on beta-blockers may not manifest changes in heart rate, but blood pressure monitoring can detect a transient rise in systolic blood pressure. The test dose should also contain 10 mg to 15 mg of MARCAINE or an equivalent amount of another local anesthetic to detect an unintended intrathecal administration. This will be evidenced within a few minutes by signs of spinal block (e.g., decreased sensation of the buttocks, paresis of the legs, or, in the sedated patient, absent knee jerk). The Test Dose formulation of MARCAINE contains 15 mg of bupivacaine and 15 mcg of epinephrine in a volume of 3 mL. An intravascular or subarachnoid injection is still possible even if results of the test dose are negative. The test dose itself may produce a systemic toxic reaction, high spinal or epinephrine-induced cardiovascular effects.

Injection of repeated doses of local anesthetics may cause significant increases in plasma levels with each repeated dose due to slow accumulation of the drug or its metabolites, or to slow metabolic degradation. Tolerance to elevated blood levels varies with the status of the patient. Debilitated, elderly patients and acutely ill patients should be given reduced doses commensurate with their age and physical status. Local anesthetics should also be used with caution in patients with hypotension or heartblock.

Careful and constant monitoring of cardiovascular and respiratory (adequacy of ventilation) vital signs and the patient’s state of consciousness should be performed after each local anesthetic injection. It should be kept in mind at such times that restlessness, anxiety, incoherent speech, lightheadedness, numbness and tingling of the mouth and lips, metallic taste, tinnitus, dizziness, blurred vision, tremors, twitching, depression, or drowsiness may be early warning signs of central nervous system toxicity.

Local anesthetic solutions containing a vasoconstrictor should be used cautiously and in carefully restricted quantities in areas of the body supplied by end arteries or having otherwise compromised blood supply such as digits, nose, external ear, or penis. Patients with hypertensive vascular disease may exhibit exaggerated vasoconstrictor response. Ischemic injury or necrosis may result.

Because amide-local anesthetics such as MARCAINE are metabolized by the liver, these drugs, especially repeat doses, should be used cautiously in patients with hepatic disease. Patients with severe hepatic disease, because of their inability to metabolize local anesthetics normally, are at a greater risk of developing toxic plasma concentrations. Local anesthetics should also be used with caution in patients with impaired cardiovascular function because they may be less able to compensate for functional changes associated with the prolongation of AV conduction produced by these drugs.

Serious dose-related cardiac arrhythmias may occur if preparations containing a vasoconstrictor such as epinephrine are employed in patients during or following the administration of potent inhalation anesthetics. In deciding whether to use these products concurrently in the same patient, the combined action of both agents upon the myocardium, the concentration and volume of vasoconstrictor used, and the time since injection, when applicable, should be taken into account.

Many drugs used during the conduct of anesthesia are considered potential triggering agents for familial malignant hyperthermia. Because it is not known whether amide-type local anesthetics may trigger this reaction and because the need for supplemental general anesthesia cannot be predicted in advance, it is suggested that a standard protocol for management should be available. Early unexplained signs of tachycardia, tachypnea, labile blood pressure, and metabolic acidosis may precede temperature elevation. Successful outcome is dependent on early diagnosis, prompt discontinuance of the suspect triggering agent(s) and prompt institution of treatment, including oxygen therapy, indicated supportive measures and dantrolene. (Consult dantrolene sodium intravenous package insert before using.)

Use in Head and Neck Area: Small doses of local anesthetics injected into the head and neck area, including retrobulbar, dental, and stellate ganglion blocks, may produce adverse reactions similar to systemic toxicity seen with unintentional intravascular injections of larger doses. The injection procedures require the utmost care. Confusion, convulsions, respiratory depression, and/or respiratory arrest, and cardiovascular stimulation or depression have been reported. These reactions may be due to intra-arterial injection of the local anesthetic with retrograde flow to the cerebral circulation. They may also be due to puncture of the dural sheath of the optic nerve during retrobulbar block with diffusion of any local anesthetic along the subdural space to the midbrain. Patients receiving these blocks should have their circulation and respiration monitored and be constantly observed. Resuscitative equipment and personnel for treating adverse reactions should be immediately available. Dosage recommendations should not be exceeded. (See DOSAGE AND ADMINISTRATION.)

Use in Ophthalmic Surgery: Clinicians who perform retrobulbar blocks should be aware that there have been reports of respiratory arrest following local anesthetic injection. Prior to retrobulbar block, as with all other regional procedures, the immediate availability of equipment, drugs, and personnel to manage respiratory arrest or depression, convulsions, and cardiac stimulation or depression should be assured (see also WARNINGS and Use In Head and Neck Area, above). As with other anesthetic procedures, patients should be constantly monitored following ophthalmic blocks for signs of these adverse reactions, which may occur following relatively low total doses.

A concentration of 0.75% bupivacaine is indicated for retrobulbar block; however, this concentration is not indicated for any other peripheral nerve block, including the facial nerve, and not indicated for local infiltration, including the conjunctiva (see INDICATIONS AND USAGE and PRECAUTIONS, General). Mixing MARCAINE with other local anesthetics is not recommended because of insufficient data on the clinical use of such mixtures.

When MARCAINE 0.75% is used for retrobulbar block, complete corneal anesthesia usually precedes onset of clinically acceptable external ocular muscle akinesia. Therefore, presence of akinesia rather than anesthesia alone should determine readiness of the patient for surgery.

Use in Dentistry: Because of the long duration of anesthesia, when MARCAINE 0.5% with epinephrine is used for dental injections, patients should be cautioned about the possibility of inadvertent trauma to tongue, lips, and buccal mucosa and advised not to chew solid foods or test the anesthetized area by biting or probing.

PATIENT COUNSELING INFORMATION

Information for Patients: When appropriate, patients should be informed in advance that they may experience temporary loss of sensation and motor activity, usually in the lower half of the body, following proper administration of caudal or epidural anesthesia. Also, when appropriate, the physician should discuss other information including adverse reactions in the package insert of MARCAINE.

Patients receiving dental injections of MARCAINE should be cautioned not to chew solid foods or test the anesthetized area by biting or probing until anesthesia has worn off (up to 7 hours).

DRUG INTERACTIONS

Clinically Significant Drug Interactions: The administration of local anesthetic solutions containing epinephrine or norepinephrine to patients receiving monoamine oxidase inhibitors or tricyclic antidepressants may produce severe, prolonged hypertension. Concurrent use of these agents should generally be avoided. In situations when concurrent therapy is necessary, careful patient monitoring is essential.

Concurrent administration of vasopressor drugs and of ergot-type oxytocic drugs may cause severe, persistent hypertension or cerebrovascular accidents.

Phenothiazines and butyrophenones may reduce or reverse the pressor effect of epinephrine.

CARCINOGENESIS AND MUTAGENESIS AND IMPAIRMENT OF FERTILITY

Carcinogenesis, Mutagenesis, Impairment of Fertility: Long-term studies in animals to evaluate the carcinogenic potential of bupivacaine hydrochloride have not been conducted. The mutagenic potential and the effect on fertility of bupivacaine hydrochloride have not been determined.

PREGNANCY

Pregnancy Category C: There are no adequate and well-controlled studies in pregnant women. MARCAINE should be used during pregnancy only if the potential benefit justifies the potential risk to the fetus. Bupivacaine hydrochloride produced developmental toxicity when administered subcutaneously to pregnant rats and rabbits at clinically relevant doses. This does not exclude the use of MARCAINE at term for obstetrical anesthesia or analgesia. (See Labor and Delivery)

Bupivacaine hydrochloride was administered subcutaneously to rats at doses of 4.4, 13.3, & 40 mg/kg and to rabbits at doses of 1.3, 5.8, & 22.2 mg/kg during the period of organogenesis (implantation to closure of the hard palate). The high doses are comparable to the daily maximum recommended human dose (MRHD) of 400 mg/day on a mg/m^2 body surface area (BSA) basis. No embryo-fetal effects were observed in rats at the high dose which caused increased maternal lethality. An increase in embryo-fetal deaths was observed in rabbits at the high dose in the absence of maternal toxicity with the fetal No Observed Adverse Effect Level representing approximately 1/5th the MRHD on a BSA basis.

In a rat pre- and post-natal development study (dosing from implantation through weaning) conducted at subcutaneous doses of 4.4, 13.3, & 40 mg/kg mg/kg/day, decreased pup survival was observed at the high dose. The high dose is comparable to the daily MRHD of 400 mg/day on a BSA basis.

Labor and Delivery: SEE BOXED WARNING REGARDING OBSTETRlCAL USE OF 0.75% MARCAINE.

MARCAINE is contraindicated for obstetrical paracervical block anesthesia.

Local anesthetics rapidly cross the placenta, and when used for epidural, caudal, or pudendal block anesthesia, can cause varying degrees of maternal, fetal, and neonatal toxicity. (See CLINICAL PHARMACOLOGY, Pharmacokinetics.) The incidence and degree of toxicity depend upon the procedure performed, the type, and amount of drug used, and the technique of drug administration. Adverse reactions in the parturient, fetus, and neonate involve alterations of the central nervous system, peripheral vascular tone, and cardiac function.

Maternal hypotension has resulted from regional anesthesia. Local anesthetics produce vasodilation by blocking sympathetic nerves. Elevating the patient’s legs and positioning her on her left side will help prevent decreases in blood pressure. The fetal heart rate also should be monitored continuously and electronic fetal monitoring is highly advisable.

Epidural, caudal, or pudendal anesthesia may alter the forces of parturition through changes in uterine contractility or maternal expulsive efforts. Epidural anesthesia has been reported to prolong the second stage of labor by removing the parturient’s reflex urge to bear down or by interfering with motor function. The use of obstetrical anesthesia may increase the need for forceps assistance.

The use of some local anesthetic drug products during labor and delivery may be followed by diminished muscle strength and tone for the first day or two of life. This has not been reported with bupivacaine.

It is extremely important to avoid aortocaval compression by the gravid uterus during administration of regional block to parturients. To do this, the patient must be maintained in the left lateral decubitus position or a blanket roll or sandbag may be placed beneath the right hip and gravid uterus displaced to the left.

NURSING MOTHERS

Nursing Mothers: Bupivacaine has been reported to be excreted in human milk suggesting that the nursing infant could be theoretically exposed to a dose of the drug. Because of the potential for serious adverse reactions in nursing infants from bupivacaine, a decision should be made whether to discontinue nursing or not administer bupivacaine, taking into account the importance of the drug to the mother.

PEDIATRIC USE

Pediatric Use: Until further experience is gained in pediatric patients younger than 12 years, administration of MARCAINE in this age group is not recommended. Continuous infusions of bupivacaine in children have been reported to result in high systemic levels of bupivacaine and seizures; high plasma levels may also be associated with cardiovascular abnormalities. (See WARNINGS, PRECAUTIONS, and OVERDOSAGE.)

GERIATRIC USE

Geriatric Use: Patients over 65 years, particularly those with hypertension, may be at increased risk for developing hypotension while undergoing anesthesia with MARCAINE. (See ADVERSE REACTIONS.)

Elderly patients may require lower doses of MARCAINE. (See PRECAUTIONS, Epidural Anesthesia and DOSAGE AND ADMINISTRATION.)

In clinical studies, differences in various pharmacokinetic parameters have been observed between elderly and younger patients. (See CLINICAL PHARMACOLOGY.)

This product is known to be substantially excreted by the kidney, and the risk of toxic reactions to this drug may be greater in patients with impaired renal function. Because elderly patients are more likely to have decreased renal function, care should be taken in dose selection, and it may be useful to monitor renal function. (See CLINICAL PHARMACOLOGY.)

ADVERSE REACTIONS

Reactions to MARCAINE are characteristic of those associated with other amide-type local anesthetics. A major cause of adverse reactions to this group of drugs is excessive plasma levels, which may be due to overdosage, unintentional intravascular injection, or slow metabolic degradation.

The most commonly encountered acute adverse experiences which demand immediate counter-measures are related to the central nervous system and the cardiovascular system. These adverse experiences are generally dose related and due to high plasma levels which may result from overdosage, rapid absorption from the injection site, diminished tolerance, or from unintentional intravascular injection of the local anesthetic solution. In addition to systemic dose-related toxicity, unintentional subarachnoid injection of drug during the intended performance of caudal or lumbar epidural block or nerve blocks near the vertebral column (especially in the head and neck region) may result in underventilation or apnea (“Total or High Spinal”). Also, hypotension due to loss of sympathetic tone and respiratory paralysis or underventilation due to cephalad extension of the motor level of anesthesia may occur. This may lead to secondary cardiac arrest if untreated. Patients over 65 years, particularly those with hypertension, may be at increased risk for experiencing the hypotensive effects of MARCAINE. Factors influencing plasma protein binding, such as acidosis, systemic diseases which alter protein production, or competition of other drugs for protein binding sites, may diminish individual tolerance.

Central Nervous System Reactions: These are characterized by excitation and/or depression. Restlessness, anxiety, dizziness, tinnitus, blurred vision, or tremors may occur, possibly proceeding to convulsions. However, excitement may be transient or absent, with depression being the first manifestation of an adverse reaction. This may quickly be followed by drowsiness merging into unconsciousness and respiratory arrest. Other central nervous system effects may be nausea, vomiting, chills, and constriction of the pupils.

The incidence of convulsions associated with the use of local anesthetics varies with the procedure used and the total dose administered. In a survey of studies of epidural anesthesia, overt toxicity progressing to convulsions occurred in approximately 0.1% of local anesthetic administrations.

Cardiovascular System Reactions: High doses or unintentional intravascular injection may lead to high plasma levels and related depression of the myocardium, decreased cardiac output, heartblock, hypotension, bradycardia, ventricular arrhythmias, including ventricular tachycardia and ventricular fibrillation, and cardiac arrest. (See WARNINGS, PRECAUTIONS, and OVERDOSAGE.)

Allergic: Allergic-type reactions are rare and may occur as a result of sensitivity to the local anesthetic or to other formulation ingredients, such as the antimicrobial preservative methylparaben contained in multiple-dose vials or sulfites in epinephrine-containing solutions. These reactions are characterized by signs such as urticaria, pruritus, erythema, angioneurotic edema (including laryngeal edema), tachycardia, sneezing, nausea, vomiting, dizziness, syncope, excessive sweating, elevated temperature, and possibly, anaphylactoid-like symptomatology (including severe hypotension). Cross sensitivity among members of the amide-type local anesthetic group has been reported. The usefulness of screening for sensitivity has not been definitely established.

Neurologic: The incidences of adverse neurologic reactions associated with the use of local anesthetics may be related to the total dose of local anesthetic administered and are also dependent upon the particular drug used, the route of administration, and the physical status of the patient. Many of these effects may be related to local anesthetic techniques, with or without a contribution from the drug.

In the practice of caudal or lumbar epidural block, occasional unintentional penetration of the subarachnoid space by the catheter or needle may occur. Subsequent adverse effects may depend partially on the amount of drug administered intrathecally and the physiological and physical effects of a dural puncture. A high spinal is characterized by paralysis of the legs, loss of consciousness, respiratory paralysis, and bradycardia.

Neurologic effects following epidural or caudal anesthesia may include spinal block of varying magnitude (including high or total spinal block); hypotension secondary to spinal block; urinary retention; fecal and urinary incontinence; loss of perineal sensation and sexual function; persistent anesthesia, paresthesia, weakness, paralysis of the lower extremities and loss of sphincter control all of which may have slow, incomplete, or no recovery; headache; backache; septic meningitis; meningismus; slowing of labor; increased incidence of forceps delivery; and cranial nerve palsies due to traction on nerves from loss of cerebrospinal fluid.

Neurologic effects following other procedures or routes of administration may include persistent anesthesia, paresthesia, weakness, paralysis, all of which may have slow, incomplete, or no recovery.

OVERDOSAGE

Acute emergencies from local anesthetics are generally related to high plasma levels encountered during therapeutic use of local anesthetics or to unintended subarachnoid injection of local anesthetic solution. (See ADVERSE REACTIONS, WARNINGS, and PRECAUTIONS.)

Management of Local Anesthetic Emergencies: The first consideration is prevention, best accomplished by careful and constant monitoring of cardiovascular and respiratory vital signs and the patient’s state of consciousness after each local anesthetic injection. At the first sign of change, oxygen should be administered.

The first step in the management of systemic toxic reactions, as well as underventilation or apnea due to unintentional subarachnoid injection of drug solution, consists of immediate attention to the establishment and maintenance of a patent airway and effective assisted or controlled ventilation with 100% oxygen with a delivery system capable of permitting immediate positive airway pressure by mask. This may prevent convulsions if they have not already occurred.

If necessary, use drugs to control the convulsions. A 50 mg to 100 mg bolus IV injection of succinylcholine will paralyze the patient without depressing the central nervous or cardiovascular systems and facilitate ventilation. A bolus IV dose of 5 mg to 10 mg of diazepam or 50 mg to 100 mg of thiopental will permit ventilation and counteract central nervous system stimulation, but these drugs also depress central nervous system, respiratory, and cardiac function, add to postictal depression and may result in apnea. Intravenous barbiturates, anticonvulsant agents, or muscle relaxants should only be administered by those familiar with their use. Immediately after the institution of these ventilatory measures, the adequacy of the circulation should be evaluated. Supportive treatment of circulatory depression may require administration of intravenous fluids, and when appropriate, a vasopressor dictated by the clinical situation (such as ephedrine or epinephrine to enhance myocardial contractile force).

Endotracheal intubation, employing drugs and techniques familiar to the clinician, may be indicated after initial administration of oxygen by mask if difficulty is encountered in the maintenance of a patent airway, or if prolonged ventilatory support (assisted or controlled) is indicated.

Recent clinical data from patients experiencing local anesthetic-induced convulsions demonstrated rapid development of hypoxia, hypercarbia, and acidosis with bupivacaine within a minute of the onset of convulsions. These observations suggest that oxygen consumption and carbon dioxide production are greatly increased during local anesthetic convulsions and emphasize the importance of immediate and effective ventilation with oxygen which may avoid cardiac arrest.

If not treated immediately, convulsions with simultaneous hypoxia, hypercarbia, and acidosis plus myocardial depression from the direct effects of the local anesthetic may result in cardiac arrhythmias, bradycardia, asystole, ventricular fibrillation, or cardiac arrest. Respiratory abnormalities, including apnea, may occur. Underventilation or apnea due to unintentional subarachnoid injection of local anesthetic solution may produce these same signs and also lead to cardiac arrest if ventilatory support is not instituted. If cardiac arrest should occur, successful outcome may require prolonged resuscitative efforts.

The supine position is dangerous in pregnant women at term because of aortocaval compression by the gravid uterus. Therefore during treatment of systemic toxicity, maternal hypotension or fetal bradycardia following regional block, the parturient should be maintained in the left lateral decubitus position if possible, or manual displacement of the uterus off the great vessels be accomplished.

The mean seizure dosage of bupivacaine in rhesus monkeys was found to be 4.4 mg/kg with mean arterial plasma concentration of 4.5 mcg/mL. The intravenous and subcutaneous LD50 in mice is 6 mg/kg to 8 mg/kg and 38 mg/kg to 54 mg/kg respectively.

DOSAGE AND ADMINISTRATION

The dose of any local anesthetic administered varies with the anesthetic procedure, the area to be anesthetized, the vascularity of the tissues, the number of neuronal segments to be blocked, the depth of anesthesia and degree of muscle relaxation required, the duration of anesthesia desired, individual tolerance, and the physical condition of the patient. The smallest dose and concentration required to produce the desired result should be administered. Dosages of MARCAINE should be reduced for elderly and/or debilitated patients and patients with cardiac and/or liver disease. The rapid injection of a large volume of local anesthetic solution should be avoided and fractional (incremental) doses should be used when feasible.

For specific techniques and procedures, refer to standard textbooks.

There have been adverse event reports of chondrolysis in patients receiving intra-articular infusions of local anesthetics following arthroscopic and other surgical procedures. MARCAINE is not approved for this use (see WARNINGS and DOSAGE AND ADMINISTRATION).

In recommended doses, MARCAINE produces complete sensory block, but the effect on motor function differs among the three concentrations.

0.25%—when used for caudal, epidural, or peripheral nerve block, produces incomplete motor block. Should be used for operations in which muscle relaxation is not important, or when another means of providing muscle relaxation is used concurrently. Onset of action may be slower than with the 0.5% or 0.75% solutions.

0.5%— provides motor blockade for caudal, epidural, or nerve block, but muscle relaxation may be inadequate for operations in which complete muscle relaxation is essential.

0.75%—produces complete motor block. Most useful for epidural block in abdominal operations requiring complete muscle relaxation, and for retrobulbar anesthesia. Not for obstetrical anesthesia.

The duration of anesthesia with MARCAINE is such that for most indications, a single dose is sufficient.

Maximum dosage limit must be individualized in each case after evaluating the size and physical status of the patient, as well as the usual rate of systemic absorption from a particular injection site. Most experience to date is with single doses of MARCAINE up to 225 mg with epinephrine 1:200,000 and 175 mg without epinephrine; more or less drug may be used depending on individualization of each case.

These doses may be repeated up to once every three hours. In clinical studies to date, total daily doses have been up to 400 mg. Until further experience is gained, this dose should not be exceeded in 24 hours. The duration of anesthetic effect may be prolonged by the addition of epinephrine.

The dosages in Table 1 have generally proved satisfactory and are recommended as a guide for use in the average adult. These dosages should be reduced for elderly or debilitated patients. Until further experience is gained, MARCAINE is not recommended for pediatric patients younger than 12 years. MARCAINE is contraindicated for obstetrical paracervical blocks, and is not recommended for intravenous regional anesthesia (Bier Block).

Use in Epidural Anesthesia: During epidural administration of MARCAINE, 0.5% and 0.75% solutions should be administered in incremental doses of 3 mL to 5 mL with sufficient time between doses to detect toxic manifestations of unintentional intravascular or intrathecal injection. In obstetrics, only the 0.5% and 0.25% concentrations should be used; incremental doses of 3 mL to 5 mL of the 0.5% solution not exceeding 50 mg to 100 mg at any dosing interval are recommended. Repeat doses should be preceded by a test dose containing epinephrine if not contraindicated. Use only the single-dose ampuls and single-dose vials for caudal or epidural anesthesia; the multiple-dose vials contain a preservative and therefore should not be used for these procedures.

Test Dose for Caudal and Lumbar Epidural Blocks: The Test Dose of MARCAINE (0.5% bupivacaine with 1:200,000 epinephrine in a 3 mL ampul) is recommended for use as a test dose when clinical conditions permit prior to caudal and lumbar epidural blocks. This may serve as a warning of unintended intravascular or subarachnoid injection. (See PRECAUTIONS.) The pulse rate and other signs should be monitored carefully immediately following each test dose administration to detect possible intravascular injection, and adequate time for onset of spinal block should be allotted to detect possible intrathecal injection. An intravascular or subarachnoid injection is still possible even if results of the test dose are negative. The test dose itself may produce a systemic toxic reaction, high spinal or cardiovascular effects from the epinephrine. (See WARNINGS and OVERDOSAGE.)

Use in Dentistry: The 0.5% concentration with epinephrine is recommended for infiltration and block injection in the maxillary and mandibular area when a longer duration of local anesthetic action is desired, such as for oral surgical procedures generally associated with significant postoperative pain. The average dose of 1.8 mL (9 mg) per injection site will usually suffice; an occasional second dose of 1.8 mL (9 mg) may be used if necessary to produce adequate anesthesia after making allowance for 2 to 10 minutes onset time. (See CLINICAL PHARMACOLOGY.) The lowest effective dose should be employed and time should be allowed between injections; it is recommended that the total dose for all injection sites, spread out over a single dental sitting, should not ordinarily exceed 90 mg for a healthy adult patient (ten 1.8 mL injections of 0.5% MARCAINE with epinephrine). Injections should be made slowly and with frequent aspirations. Until further experience is gained, MARCAINE in dentistry is not recommended for pediatric patients younger than 12 years.

Unused portions of solution not containing preservatives, i.e., those supplied in single-dose ampuls and single-dose vials, should be discarded following initial use.

This product should be inspected visually for particulate matter and discoloration prior to administration whenever solution and container permit. Solutions which are discolored or which contain particulate matter should not be administered.

Table 1. Recommended Concentrations and Doses of MARCAINE
Type of Block | Conc. | Each Dose |  | Motor Block^1
Type of Block | Conc. | (mL) | (mg) | Motor Block^1
Local; infiltration | 0.25%^4 | up to max. | up to max. | —
Epidural | 0.75%^2,4 | 10-20 | 75-150 | complete
Epidural | 0.5%^4 | 10-20 | 50-100 | moderate to complete
Epidural | 0.25%^4 | 10-20 | 25-50 | partial to moderate
Caudal | 0.5%^4 | 15-30 | 75-150 | moderate to complete
Caudal | 0.25%^4 | 15-30 | 37.5-75 | moderate
Peripheral nerves | 0.5%^4 | 5 to max. | 25 to max. | moderate to complete
Peripheral nerves | 0.25%^4 | 5 to max. | 12.5 to max. | moderate to complete
Retrobulbar^3 | 0.75%^4 | 2-4 | 15-30 | complete
Sympathetic | 0.25% | 20-50 | 50-125 | —
Dental^3 | 0.5% w/epi | 1.8-3.6 per site | 9-18 per site | —
Epidural^3 Test Dose | 0.5% w/epi | 2-3 | 10-15 (10-15 micrograms epinephrine) | —
^1With continuous (intermittent) techniques, repeat doses increase the degree of motor block. The first repeat dose of 0.5% may produce complete motor block. Intercostal nerve block with 0.25% may also produce complete motor block for intra-abdominal surgery.
^2For single-dose use, not for intermittent epidural technique. Not for obstetrical anesthesia.
^3See PRECAUTIONS.
^4Solutions with or without epinephrine.

HOW SUPPLIED

These solutions are not for spinal anesthesia.

Store at 20 to 25°C (68 to 77°F). [See USP Controlled Room Temperature.]

MARCAINE ―Solutions of MARCAINE that do not contain epinephrine may be autoclaved. Autoclave at 15-pound pressure, 121°C (250°F) for 15 minutes.

NDC No. | Container | Fill | Quantity
 | 0.25%—Contains 2.5 mg bupivacaine hydrochloride per mL.
0409-1559-10 | Single-dose vials | 10 mL | box of 10
0409-1559-30 | Single-dose vials | 30 mL | box of 10
0409-1587-50 | Multiple-dose vials | 50 mL | box of 1
 | 0.5%—Contains 5 mg bupivacaine hydrochloride per mL.
0409-1560-10 | Single-dose vials | 10 mL | box of 10
0409-1560-29 | Single-dose vials | 30 mL | box of 10
0409-1610-50 | Multiple-dose vials | 50 mL | box of 1
 | 0.75%—Contains 7.5 mg bupivacaine hydrochloride per mL.
0409-1582-10 | Single-dose vials | 10 mL | box of 10
0409-1582-29 | Single-dose vials | 30 mL | box of 10

MARCAINE with epinephrine 1:200,000 (as bitartrate)―Solutions of MARCAINE that contain epinephrine should not be autoclaved and should be protected from light. Do not use the solution if its color is pinkish or darker than slightly yellow or if it contains a precipitate.

NDC No. | Container | Fill | Quantity
0.25% with epinephrine 1:200,000—Contains 2.5 mg bupivacaine hydrochloride per mL.
0409-1746-10 | Single-dose vials | 10 mL | box of 10
0409-1746-30 | Single-dose vials | 30 mL | box of 10
0409-1752-50 | Multiple-dose vials | 50 mL | box of 1
0.5% with epinephrine 1:200,000—Contains 5 mg bupivacaine hydrochloride per mL.
0409-1749-03 | Single-dose ampuls | 3 mL | box of 10
0409-1749-10 | Single-dose vials | 10 mL | box of 10
0409-1749-29 | Single-dose vials | 30 mL | box of 10
0409-1755-50 | Multiple-dose vials | 50 mL | box of 1

Revised: 10/2011

Printed in USA EN-2916

Hospira, Inc., Lake Forest, IL 60045 USA

NOT FOR USE IN NEONATES CONTAINS BENZYL ALCOHOL

Not For Intravenous Use

DESCRIPTION

Methylprednisolone acetate injectable suspension, USP is an anti-inflammatory glucocorticoid for intramuscular, intra-articular, soft tissue or intralesional injection. It is available in two strengths: 40 mg/mL; 80 mg/mL

Each mL of these preparations contains:

Methylprednisolone acetate………………………………….. | 40 mg | 80 mg
Polyethylene glycol 3350…………………………………….. | 29.1 mg | 28.2 mg
Polysorbate 80…………………………………….………... | 1.94 mg | 1.88 mg
Monobasic sodium phosphate……………………………….. | 6.8 mg | 6.59 mg
Dibasic sodium phosphate USP……………………………… | 1.42 mg | 1.37 mg
Benzyl alcohol added as a preservative………………………. | 9.16 mg | 8.88 mg

Sodium Chloride was added to adjust tonicity.

When necessary, pH was adjusted with sodium hydroxide and/or hydrochloric acid.

The pH of the finished product remains within the USP specified range; e.g., 3.0 to 7.0.

The chemical name for methylprednisolone acetate is pregna-1,4-diene-3,20-dione, 21-(acetyloxy)-11,17-dihydroxy-6-methyl-,(6α,11β)-and the molecular weight is 416.51. The structural formula is represented below:

Methylprednisolone acetate injectable suspension, USP contains methylprednisolone acetate which is the 6-methyl derivative of prednisolone. Methylprednisolone acetate is a white or practically white, odorless, crystalline powder which melts at about 215° with some decomposition. It is soluble in dioxane, sparingly soluble in acetone, in alcohol, in chloroform, and in methanol, and slightly soluble in ether. It is practically insoluble in water.

CLINICAL PHARMACOLOGY

Glucocorticoids, naturally occurring and synthetic are adrenocortical steroids.

Naturally occurring glucocorticoids (hydrocortisone and cortisone), which also have salt retaining properties, are used in replacement therapy in adrenocortical deficiency states. Their synthetic analogs are used primarily for their anti-inflammatory effects in disorders of many organ systems.

Glucocorticoids cause profound and varied metabolic effects. In addition, they modify the body's immune response to diverse stimuli.

INDICATIONS AND USAGE

A. For Intramuscular Administration

When oral therapy is not feasible and the strength, dosage form, and route of administration of the drug reasonably lend the preparation to the treatment of the condition, the intramuscular use of methylprednisolone acetate injectable suspension, USP is indicated as follows:

Allergic States: Control of severe or incapacitating allergic conditions intractable to adequate trials of conventional treatment in asthma, atopic dermatitis, contact dermatitis, drug hypersensitivity reactions, seasonal or perennial allergic rhinitis, serum sickness, transfusion reactions.

Dermatologic Diseases: Bullous dermatitis herpetiformis, exfoliative erythroderma, mycosis fungoides, pemphigus, severe erythema multiforme (Stevens-Johnson syndrome).

Endocrine Disorders: Primary or secondary adrenocortical insufficiency (hydrocortisone or cortisone is the drug of choice; synthetic analogs may be used in conjunction with mineralocorticoids where applicable; in infancy, mineralocorticoid supplementation is of particular importance) congenital adrenal hyperplasia, hypercalcemia associated with cancer, nonsuppurative thyroiditis.

Gastrointestinal Diseases: To tide the patient over a critical period of the disease in regional enteritis (systemic therapy), ulcerative colitis.

Hematologic Disorders: Acquired (autoimmune) hemolytic anemia, congenital (erythroid) hypoplastic anemia (Diamond blackfan anemia), pure red cell aplasia, select cases of secondary thrombocytopenia.

Miscellaneous: Trichinosis with neurologic or myocardial involvement, tuberculous meningitis with subarachnoid block or impending block when used concurrently with appropriate antituberculous chemotherapy.

Neoplastic Diseases: For palliative management of leukemias and lymphomas.

Nervous System: Acute exacerbations of multiple sclerosis. Cerebral edema associated with primary or metastatic brain tumor or craniotomy.

Ophthalmic Diseases: Sympathetic ophthalmia, temporal arteritis, Uveitis and ocular inflammatory conditions unresponsive to topical corticosteroids.

Renal Diseases: To induce diuresis or remission of proteinuria in idiopathic nephrotic syndrome, or that due to lupus erythematosus.

Respiratory Diseases: Berylliosis, symptomatic sarcoidosis, fulminating or disseminated pulmonary tuberculosis when used concurrently with appropriate antituberculous chemotherapy, idiopathic eosinophilic pneumonias, symptomatic sarcoidosis.

Rheumatic Disorders: As adjunctive therapy for short-term administration (to tide the patient over an acute episode or exacerbation) in acute gouty arthritis, acute rheumatic carditis, ankylosing spondylitis, psoriatic arthritis, rheumatoid arthritis, including juvenile rheumatoid arthritis (selected cases may require low-dose maintenance therapy). For the treatment of dermatomyositis, polymyositis, and systemic lupus erythematosus.

B. For Intra-articular or Soft Tissue Administration

(See WARNINGS)

Methylprednisolone acetate injectable suspension, USP is indicated as adjunctive therapy for short-term administration (to tide the patient over an acute episode or exacerbation) in acute gouty arthritis, acute and subacute bursitis, acute nonspecific tenosynovitis, epicondylitis, rheumatoid arthritis, synovitis of osteoarthritis.

C. For Intralesional Administration

Methylprednisolone acetate injectable suspension, USP is indicated for intralesional use in alopecia areata, discoid lupus erythematosus, keloids, localized hypertrophic, infiltrated, inflammatory lesions of granuloma annulare, lichen planus, lichen simplex chronicus (neurodermatitis), and psoriatic plaques, necrobiosis lipoidica diabeticorum.

Methylprednisolone acetate injectable suspension, USP also may be useful in cystic tumors of an aponeurosis or tendon (ganglia).

CONTRAINDICATIONS

Methylprednisolone acetate injectable suspension, USP is contraindicated in patients with known hypersensitivity to the product and its constituents.

Intramuscular corticosteroid preparations are contraindicated for idiopathic thrombocytopenic purpura.

Methylprednisolone acetate injectable suspension, USP is contraindicated for intrathecal administration. Reports of severe medical events have been associated with this route of administration.

Methylprednisolone acetate injectable suspension, USP is contraindicated for use in premature infants because the formulation contains benzyl alcohol. (See WARNINGS and PRECAUTIONS:Pediatric Use)

Methylprednisolone acetate injectable suspension, USP is contraindicated in systemic fungal infections, except when administered as an intra-articular injection for localized joint conditions (see WARNINGS, Infections, Fungal Infections)

WARNINGS

General

This product contains benzyl alcohol which is potentially toxic when administered locally to neural tissue. Exposure to excessive amounts of benzyl alcohol has been associated with toxicity (hypotension, metabolic acidosis), particularly in neonates, and an increased incidence of kernicterus, particularly in small preterm infants. There have been rare reports of deaths, primarily in preterm infants, associated with exposure to excessive amounts of benzyl alcohol. The amount of benzyl alcohol from medications is usually considered negligible compared to that received in flush solutions containing benzyl alcohol. Administration of high dosages of medications containing this preservative must take into account the total amount of benzyl alcohol administered. The amount of benzyl alcohol at which toxicity may occur is not known. If the patient requires more than the recommended dosages or other medications containing this preservative, the practitioner must consider the daily metabolic load of benzyl alcohol from these combined sources (see PRECAUTIONS: Pediatric Use)

Multidose use of methylprednisolone acetate injectable suspension, USP from a single vial requires special care to avoid contamination. Although initially sterile, any multidose use of vials may lead to contamination unless strict aseptic technique is observed. Particular care, such as use of disposable sterile syringes and needles is necessary.

Injection of methylprednisolone acetate injectable suspension, USP may result in dermal and/or subdermal changes forming depressions in the skin at the injection site.

In order to minimize the incidence of dermal and subdermal atrophy, care must be exercised not to exceed recommended doses in injections. Multiple small injections into the area of the lesion should be made whenever possible. The technique of intra-articular and intramuscular injection should include precautions against injection or leakage into the dermis. Injection into the deltoid muscle should be avoided because of a high incidence of subcutaneous atrophy.

It is critical that, during administration of methylprednisolone acetate injectable suspension, USP, appropriate technique be used and care taken to assure proper placement of drug.

Rare instances of anaphylactoid reactions have occurred in patients receiving corticosteroid therapy. (see ADVERSE REACTIONS)

Increased dosage of rapidly acting corticosteroids is indicated in patients on corticosteroid therapy subjected to any unusual stress before, during, or after the stressful situation.

Results from one multicenter, randomized, placebo controlled study with methylprednisolone hemisuccinate, an IV corticosteroid, showed an increase in early (at 2 weeks) and late (at 6 months) mortality in patients with cranial trauma who were determined not to have other clear indications for corticosteroid treatment. High doses of systemic corticosteroids, including methylprednisolone acetate injectable suspension, USP, should not be used for the treatment of traumatic brain injury.

Cardio-renal

Average and large doses of corticosteroids can cause elevation of blood pressure, salt and water retention, and increased excretion of potassium. These effects are less likely to occur with the synthetic derivatives except when used in large doses. Dietary salt restriction and potassium supplementation may be necessary. All corticosteroids increase calcium excretion.

Literature reports suggest an apparent association between the use of corticosteroids and left ventricular free wall rupture after a recent myocardial infarction; therefore, therapy with corticosteroids should be used with great caution in these patients.

Endocrine

Hypothalamic-pituitary adrenal (HPA) axis suppression. Cushing's syndrome, and hyperglycemia. Monitor patients for these conditions with chronic use.

Corticosteroids can produce reversible HPA axis suppression with the potential for glucocorticosteroid insufficiency after withdrawal of treatment. Drug induced secondary adrenocortical insufficiency may be minimized by gradual reduction of dosage. This type of relative insufficiency may persist for months after discontinuation of therapy; therefore, in any situation of stress occurring during that period, hormone therapy should be reinstituted.

Infections

General

Persons who are on corticosteroids are more susceptible to infections than are healthy individuals. There may be decreased resistance and inability to localize infection when corticosteroids are used. Infections with any pathogen (viral, fungal, protozoan, or helminthic), in any location of the body may be associated with the use of corticosteroids alone or in combination with other immunosuppressive agents.

These infections may be mild, but can be severe and at times fatal. With increasing doses of corticosteroids, the rate of occurrence of infectious complications increases. Corticosteroids may mask some signs of current infection. Do not use intra-articularly, intrabursally or for intratendinous administration for local effect in the presence of acute local infection.

Fungal Infections

Corticosteroids may exacerbate systemic fungal infections and therefore should not be used in the presence of such infections unless they are needed to control drug reactions. There have been cases reported in which concomitant use of amphotericin B and hydrocortisone was followed by cardiac enlargement and congestive heart failure (see CONTRAINDICATIONS and PRECAUTIONS, Drug Interactions, Amphotericin B injections and potassium depleting agents)

Special pathogens

Latent disease may be activated or there may be an exacerbation of intercurrent infections due to pathogens, including those caused by Amoeba, Candida, Cryptococcus, Mycobacterium, Nocardia, Pneumocystis, Taxoplasma.

It is recommended that latent amebiasis or active amebiasis be ruled out before initiating corticosteroid therapy in any patient who has spent time in the tropics or in any patient with unexplained diarrhea.

Similarly, corticosteroids should be used with great care in patients with known or suspected Strongyloides (threadworm) infestation. In such patients, corticosteroid-induced immunosuppression may lead to Stronglyoides hyperinfection and dissemination with widespread larval migration, often accompanied by severe entercolitis and potentially fatal gram-negative septicemia.

Corticosteroids should not be used in cerebral malaria. There is currently no evidence of benefit from steroids in this condition.

Tuberculosis

The use of corticosteroids in active tuberculosis should be restricted to those cases of fulminating or disseminated tuberculosis in which the corticosteroid is used for the management of the disease in conjunction with an appropriate antituberculous regimen.

If corticosteroids are indicated in patients with latent tuberculosis or tuberculin reactivity, close observation is necessary as reactivation of the disease may occur. During prolonged corticosteroid therapy, these patients should receive chemoprophylaxis.

Vaccinations

Administration of live or live, attenuated vaccines is contraindicated in patients receiving immunosuppressive doses of corticosteroids. Killed or inactivated vaccines may be administered. However, the response to such vaccines can not be predicted. Immunization procedures may be undertaken in patients who are receiving corticosteroids, as replacement therapy, e.g. for Addison's disease.

Viral Infections

Chicken pox and measles can have a more serious or even fatal course in pediatric and adult patients on corticosteroids. In pediatric and adult patients who have not had these diseases, particular care should be taken to avoid exposure. The contribution of the underlying disease and/or prior corticosteroid treatment to the risk is also not known. If exposed to chicken pox, prophylaxis with varicella zoster immune globulin (VZIG) may be indicated. If exposed to measles, prophylaxis with immunoglobulin (IG) may be indicated. (See the respective package inserts for complete VZIG and IG prescribing information.) If chicken pox develops, treatment with antiviral agents should be considered.

Ophthalmic

Use of corticosteroids may produce posterior subcapsular cataracts, glaucoma with possible damage to the optic nerves, and may enhance the establishment of secondary ocular infections due to bacteria, fungi or viruses. The use of systemic corticosteroids is not recommended in the treatment of optic neuritis and may lead to an increase in the risk of new episodes. Corticosteroids should be used cautiously in patients with active ocular herpes simplex because of corneal perforation. Corticosteroids should not be used in active ocular herpes simplex.

PRECAUTIONS

General

When multidose vials are used, special care to prevent contamination of the contents is essential. A povidone-iodine solution or similar product is recommended to cleanse the vial top prior to aspiration of contents. (See WARNINGS)

This product, like many other steroid formulations, is sensitive to heat. Therefore, it should not be autoclaved when it is desirable to sterilize the outside of the vial.

The lowest possible dose of corticosteroid should be used to control the condition under treatment. When reduction in dosage is possible, the reduction should be gradual.

Since complications of treatment with glucocorticosteroids are dependent on the size of the dose and duration of treatment, a risk/benefit decision must be made in each individual case as to dose and duration of treatment and as to whether daily or intermittent therapy should be used.

Kaposi's sarcoma has been reported to occur in patients receiving corticosteroid therapy, most often for chronic conditions. Discontinuation of corticosteroids may result in clinical improvement.

Cardio-renal

As sodium retention with resultant edema and potassium loss may occur in patients receiving corticosteroids, these agents should be used with caution in patients with congestive heart failure, hypertension, or renal insufficiency.

Endocrine

Drug-induced secondary adrenocortical insufficiency may be minimized by gradual reduction of dosage. This type of relative insufficiency may persist for months after discontinuation of therapy; therefore, in any situation of stress occurring during that period, hormone therapy should be reinstituted. Since mineral corticosteroid secretion may be impaired, salt and/or a mineral corticosteroid should be administered concurrently.

Metabolic clearance of corticosteroids is decreased in hypothyroid patients and increased in hyperthyroid patients. Changes in thyroid status of the patient may necessitate adjustment in dosage.

Gastrointestinal

Steroids should be used in caution in active or latent peptic ulcer, diverticulitis, fresh intestinal anastomoses, and non-specific ulcerative colitis, since they may increase the risk of a perforation.

Signs of peritoneal irritation following gastrointestinal perforation in patients receiving corticosteroids may be minimal or absent.

There is an enhanced effect due to increased metabolism of corticosteroids in patients with cirrhosis.

Parenteral Administration

Intra-articular injected corticosteroids may be systemically absorbed.

Appropriate examination of any joint fluid is necessary to exclude a septic process.

A marked increase in pain associated by local swelling, further restriction of joint motion, fever, malaise are suggestive of septic arthritis. If this complication occurs and the diagnosis of sepsis is confirmed, appropriate antimicrobial therapy should be instituted.

Injection of a steroid into an infected site is to be avoided. Local injection of a steroid into a previously infected joint is not usually recommended.

Musculoskeletal

Corticosteroids decrease bone formation and increase bone resorption both through their effect on calcium regulation (e.g., decreasing absorption and increasing excretion) and inhibition of osteoblast function. This, together with a decrease in protein matrix of the bone secondary to an increase in protein catabolism, and reduced sex hormone production, may lead to inhibition of bone growth in pediatric patients and the development of osteoporosis at any age (e.g., postmenopausal women) before initiating corticosteroid therapy.

Neuro-psychiatric

Although controlled clinical trials have shown corticosteroids to be effective in speeding the resolution of acute exacerbations of multiple sclerosis, they do not show that corticosteroids affect the ultimate outcome or natural history of the disease. The studies do show that relatively high doses of corticosteroids are necessary to demonstrate a significant effect. (See DOSAGE AND ADMINISTRATION)

An acute myopathy has been observed with the use of high doses of corticosteroids, most often occurring in patients with disorders of neuromuscular transmission (e.g., myasthenia gravis), or in patients receiving concomitant therapy with neuromuscular blocking drugs (e.g., pancuronium). This acute myopathy is generalized, may involve ocular and respiratory muscles, and may results in quadriparesis. Elevation of creatine kinase may occur. Clinical improvement or recovery after stopping corticosteroids may require weeks to years.

Psychic derangements may appear when corticosteroids are used, ranging from euphoria, insomnia, mood swings, personality changes, and severe depression to frank psychotic manifestations. Also, existing emotional instability or psychotic tendencies may be aggravated by corticosteroids.

Ophthalmic

Intraocular pressure may become elevated in some individuals. If steroid therapy is continued for more than 6 weeks, intraocular pressure should be monitored.

Corticosteroids should be used cautiously in patients with ocular herpes simplex for fear of corneal perforation.

Information for the Patient

Patients should be warned not to discontinue the use of corticosteroids abruptly or without medical supervision, to advise any medical attendants that they are taking corticosteroids and to seek medical advice at once should they develop fever or other signs of infection.

Persons who are on corticosteroids should be warned to avoid exposure to chicken pox or measles. Patients should also be advised that if they are exposed, medical advice should be sought without delay.

DRUG INTERACTIONS

Aminoglutethimide

Aminoglutethimide may lead to a loss of corticosteroid-induced adrenal suppression.

Amphotericin B injection and potassium- depleting agents

When corticosteroids are administered concomitantly with potassium-depleting agents (e.g., amphotericin B, diuretics), patients should be observed closely for development of hypokalemia. There have been cases reported in which concomitant use of amphotericin B and hydrocortisone was followed by cardiac enlargement and congestive heart failure.

Antibiotics

Macrolide antibiotics have been reported to cause significant decrease in corticosteroid clearance (see DRUG INTERACTIONS, Hepatic Enzyme Inhibitors)

Anticholinesterases

Concomitant use of anticholinesterase agents and corticosteroids may produce severe weakness in patients with myasthenia gravis. If possible, anticholinesterase agents should be withdrawn at least 24 hours before initiating corticosteroid therapy.

Anticoagulants, oral

Coadministration of corticosteroids and warfarin usually results in inhibition of response to warfarin, although there have been some conflicting reports. Therefore, coagulation indices should be monitored frequently to maintain the desired anticoagulant effect.

Antidiabetics

Because corticosteroids may increase blood glucose concentrations, dosage adjustments of antidiabetic agents may be required.

Antitubercular drugs

Serum concentrations of isoniazid may be decreased.

Cholestyramine

Cholestyramine may increase the clearance of oral corticosteroids.

Cyclosporine

Increased activity of both cyclosporine and corticosteroids may occur when the two are used concurrently. Convulsions have been reported with concurrent use.

Digitalis glycosides

Patients on digitalis glycosides may be at increased risk of arrhythmias due to hypokalemia.

Estrogens, including oral contraceptives

Estrogens may decrease the hepatic metabolism of certain corticosteroids, thereby increasing their effect.

Hepatic Enzyme Inducers (e.g., barbiturates, phenytoin, carbamazepine, rifampin)

Drugs which induce cytochrome P450 3A4 enzyme activity may enhance the metabolism of corticosteroids and require that the dosage of corticosteroid be increased.

Hepatic Enzyme Inhibitors (e.g., ketoconazole, macrolide antibiotics such as erythromycin and troleandomycin)

Drugs which inhibit cytochrome P450 3A4 have the potential to result in increased plasma concentrations of corticosteroids.

Ketoconazole

Ketoconazole has been reported to significantly decrease the metabolism of certain corticosteroids by up to 60%,, leading to an increased risk of corticosteroid side effects.

Non-steroidal anti-inflammatory agents (NSAIDs)

Concomitant use of aspirin (or other nonsteroidal anti-inflammatory agents) and corticosteroids increases the risk of gastrointestinal side-effects. Aspirin should be used cautiously in conjunction with concurrent use of corticosteroids in hypoprothrombinemia. The clearance of salicylates may be increased with concurrent use of corticosteroids.

Skin Tests

Corticosteroids may suppress reactions to skin tests.

Vaccines

Patients on prolonged corticosteroid therapy may exhibit a diminished response to toxoids and live or attenuated vaccines due to inhibition of antibody response. Corticosteroids may also potentiate the replication of some organisms contained in live attenuated vaccines. Routine administration of vaccines or toxoids should be deferred until corticosteroid therapy is discontinued if possible (see WARNINGS, Infections, Vaccinations)

Carcinogenesis, Mutagenesis, Impairment of Fertility

No adequate studies have been conducted in animals to determine whether corticosteroids have a potential for carcinogenesis or mutagenesis. Steroids may increase or decrease motility and number of spermatozoa in some patients.

Pregnancy

Teratogenic effects

Pregnancy Category C

Corticosteroids have been shown to be teratogenic in many species when given in doses equivalent to human dose. Animal studies in which corticosteroids have been given to pregnant mice, rats, and rabbits, have yielded an increase incidence of cleft palate in the off-spring. There are no adequate and well-controlled studies in pregnant women. Corticosteroids should be used during pregnancy only if the potential benefit justifies the potential risk to the fetus. Infants born to mothers who have received corticosteroids during pregnancy should be carefully observed for signs of hypoadrenalism.

Nursing Mothers

Systemically administered corticosteroids appear in human milk and could suppress growth, interfere with endogenous corticosteroid production, or cause other untoward effects. Because of the potential for serious adverse reactions in nursing infants from corticosteroids, a decision should be made whether to continue nursing, or discontinue the drug, taking into account the importance of the drug to the mother.

Pediatric Use

This product contains benzyl alcohol as a preservative. Benzyl alcohol, a component of this product, has been associated with serious adverse events and death, particularly in pediatric patients. The "gasping syndrome", (characterized by central nervous system depression, metabolic acidosis, gasping respirations, and high levels of benzyl alcohol and its metabolites found in the blood and urine) has been associated with benzyl alcohol dosages >99 mg/kg/day in neonates and low-birth-weight neonates. Additional symptoms may include gradual neurological deterioration, seizures, intracranial hemorrhage, hematologic abnormalities, skin breakdown, hepatic and renal failure, hypotension, bradycardia, and cardiovascular collapse. Although normal therapeutic doses of this product deliver amounts of benzyl alcohol that are substantially lower than those reported in association with the "gasping syndrome", the minimum amount of benzyl alcohol at which toxicity may occur is not known. Premature and low-birth-weight infants, as well as patients receiving high dosages, may be more likely to develop toxicity. Practitioners administering this and other medications containing benzyl alcohol should consider the combined daily metabolic load of benzyl alcohol from all sources.

The efficacy and safety of corticosteroids in the pediatric population are based on the well-established course of effect of corticosteroids which is similar in pediatric and adult populations. Published studies provide evidence of efficacy and safety in pediatric patients for the treatment of nephritic syndrome (patients >2 years of age), and aggressive lymphomas and leukemias (patients >1 month of age). Other indications for pediatric use of corticosteroids, e.g., severe asthma and wheezing, are based on adequate and well-controlled clinical trials conducted in adults, on the premises that the course of the diseases and their pathophysiology are considered to be substantially similar in both populations.

The adverse effects of corticosteroids in pediatric patients are similar to those in adults (see ADVERSE REACTIONS). Like adults, pediatric patients should be carefully observed with frequent measurements of blood pressure, weight, height, intraocular pressure, and clinical evaluation for the presence of infection, psychosocial disturbances, thromboembolism, peptic ulcers, cataracts, and osteoporosis. Pediatric patients who are treated with corticosteroids by any route, including systemically administered corticosteroids, may experience a decrease in their growth velocity. This negative impact of corticosteroids on growth has been observed at low systemic doses and in the absence of laboratory evidence of hypothalamic-pituitary-adrenal (HPA) axis suppression (e.g., cosyntropin stimulation and basal cortisol plasma levels). Growth velocity may therefore be a more sensitive indicator of systemic corticosteroid exposure in pediatric patients than some commonly used tests of HPA axis function. The linear growth of pediatric patients treated with corticosteroids should be monitored, and the potential growth effects of prolonged treatment should be weighed against clinical benefits obtained and the ability of treatment alternatives. In order to minimize the potential growth effects of corticosteroids, pediatric patients should be titrated to the lowest effective dose.

Geriatric Use

Clinical studies did not include sufficient numbers of subjects aged 65 and over to determine whether they respond differently from younger subjects. Other reported clinical experience has not identified differences in responses between the elderly and younger patients. In general, dose selection for an elderly patient should be cautious, usually starting at the low end of the dosing range, reflecting the greater frequency of decreased hepatic, renal, or cardiac function, and of concomitant disease or other drug therapy.

ADVERSE REACTIONS

The following adverse reactions have been reported with methylprednisolone acetate injectable suspension, USP or other corticosteroids:

Allergic reactions: Allergic or hypersensitivity reactions, anaphylactoid reaction, anaphylaxis, angioedema.

Cardiovascular: Bradycardia, cardiac arrest, cardiac arrhythmias, cardiac enlargement, circulatory collapse, congestive heart failure, fat embolism, hypertension, hypertrophic cardiomyopthy in premature infants, myocardial rupture following recent mycocardial infarction (see WARNINGS), pulmonary edema, syncope, tachycardia, thromboembolism, thrombophlebitis, vasculitis.

Dermatologic: Acne, allergic dermatitis, cutaneous and subcutaneous atrophy, dry scaly skin, ecchymoses and petechiae, edema, erythema, hyperpigmentation, hypopigmentation, impaired wound healing, increase sweating, rash, sterile abscess, striae, suppressed reactions to skin tests, thin fragile skin, thinning scalp hair, urticaria.

Endocrine: Decreased carbohydrate and glucose tolerance, development of cushingoid state, glycosuria, hirsutism, hypertrichosis, increased requirements for insulin or oral hypoglycemic agents in diabetes, manifestations of latent diabetes mellitus, menstrual irregularities, secondary adrenocortical and pituitary unresponsiveness (particularly in times of stress, as in trauma, surgery, or illness), suppression of growth in pediatric patients.

Fluid and electrolyte disturbances: Congestive heart failure in susceptible patients, Fluid retention, hypokalemic alkalosis, potassium loss, sodium retention.

Gastrointestinal: Abdominal distention, bowel/bladder dysfunction (after intrathecal administration), elevation in serum liver enzymes levels (usually reversible upon discontinuation), hepatomegaly, increased appetite, nausea, pancreatitis, peptic ulcer with possible subsequent perforation and hemorrhage, perforation of the small and large intestine (particularly in patients with inflammatory bowel disease), ulcerative esophagitis.

Metabolic: Negative nitrogen balance due to protein catabolism.

Musculoskeletal: Aseptic necrosis of femoral and humeral heads, calcinosis (following intra-articular or intra-lesional use), Charcot-like arthropathy, loss of muscle mass, muscle weakness, osteoporosis, pathologic fracture of long bones, postinjection flare (following intra-articular use), steroid myopathy, tendon rupture, vertebral compression fractures.

Neurologic/Psychiatric: Convulsions, depression, emotional instability, euphoria, headache, increased intracranial pressure with papilledema (pseudotumor cerebri) usually following discontinuation of treatment, insomnia, mood swings, neuritis, neuropathy, paresthesia, personality changes, psychic disorders, vertigo.

Ophthalmic: Exophthalmoses, glaucoma, increased intraocular pressure, posterior subcapsular cataracts.

Other: Abnormal fat deposits, decreased resistance to infection, hiccups, increased or decreased motility and number of spermatozoa, injection site infections following non-sterile administration (see WARNINGS), malaise, moon face, weight gain.

The following adverse reactions have been reported with the following routes of administration:

Intrathecal/Epidural: Arachnoiditis, bowel/bladder dysfunction, headache, meningitis, parapareisis/paraplegia, seizures, sensory disturbances.

Intranasal: Allergic reactions, rhinitis, temporary/permanent visual impairment including blindness.

Ophthalmic: Increased intraocular pressure, infection, ocular and periocular inflammation including allergic reactions, residue or slough at injection site, temporary/permanent visual impairment including blindness.

Miscellaneous injection sites: (scalp, tonsillar fauces, sphenopalatine ganglion): Blindness.

OVERDOSAGE

Treatment of acute overdosage is by supportive and symptomatic therapy. For chronic overdosage in the face of severe disease requiring continuous steroid therapy, the dosage of corticosteroid may be reduced only temporarily, or alternate day treatment may be introduced.

DOSAGE AND ADMINISTRATION

NOTE: CONTAINS BENZYL ALCOHOL (see WARNINGS and PRECAUTIONS: Pediatric Use)

Because of possible physical incompatibilities, methylprednisolone acetate injectable suspension, USP should not be diluted or mixed with other solutions.

The initial dosage of parenterally administered methylprednisolone acetate injectable suspension, USP will vary from 4 to 120 mg depending on the specific disease entity being treated. However, in certain overwhelming, acute, life-threatening situations, administrations in dosages exceeding the usual dosages may be justified and may be in multiples of the oral doses.

It Should Be Emphasized that Dosage Requirements are Variable and Must Be Individualized on the Basis of the Disease Under Treatment and the Response of the Patient. After a favorable response is noted, the proper maintenance dose should be determined by decreasing the initial drug dosage in small increments at appropriate time intervals until the lowest dosage which will maintain an adequate clinical response is reached. Situations which may make dosage adjustments necessary are changes in clinical status secondary to remissions or exacerbations in the disease process, the patient's individual drug responsiveness, and the effect of patient exposure to stressful situations not directly related to the disease entity under treatment. In this latter situation it may be necessary to increase the dosage of the corticosteroid for a period of time consistent with the patient's condition. If after long term therapy the drug is to be stopped, it is recommended that it be withdrawn gradually rather than abruptly.

A. Administration for Local Effect

Therapy with methylprednisolone acetate injectable suspension, USP does not obviate the need for the conventional measures usually employed. Although this method of treatment will ameliorate symptoms, it is in no sense a cure and the hormone has no effect on the cause of the inflammation.

1. Rheumatoid and Osteoarthritis

The dose for intra-articular administration depends upon the size of the joint and varies with the severity of the condition in the individual patient. In chronic cases, injections may be repeated at intervals ranging from one to five or more weeks depending upon the degree of relief obtained from the initial injection. The doses in the following table are given as a general guide:

Size of Joint | Examples |  | Range of Dosage
Large | Knees Ankles Shoulders |  | 20 to 80 mg
Medium | Elbows Wrists |  | 10 to 40 mg
Small | Metacarpophalangeal Interphalangeal Sternoclavicular Acromioclavicular |  | 4 to 10 mg

Procedure

It is recommended that the anatomy of the joint involved be reviewed before attempting intra-articular injection. In order to obtain the full anti-inflammatory effect it is important that the injection be made into the synovial space. Employing the same sterile technique as for a lumbar puncture, a sterile 20 to 24 gauge needle (on a dry syringe) is quickly inserted into the synovial cavity. Procaine infiltration is elective. The aspiration of only a few drops of joint fluid proves the joint space has been entered by the needle. The injection site for each joint is determined by that location where the synovial cavity is most superficial and most free of large vessels and nerves. With the needle in place, the aspirating syringe is removed and replaced by a second syringe containing the desired amount of methylprednisolone acetate injectable suspension, USP. The plunger is then pulled outward slightly to aspirate synovial fluid and to make sure the needle is still in the synovial space. After injection, the joint is moved gently a few times to aid mixing of the synovial fluid and the suspension. The site is covered with a small sterile dressing.

Suitable sites for intra-articular injection are the knee, ankle, wrist, elbow, shoulder, phalangeal, and hip joints. Since difficulty is not infrequently encountered in entering the hip joint, precautions should be taken to avoid any large blood vessels in the area. Joints not suitable for injection are those that are anatomically inaccessible such as the spinal joints and those like the sacroiliac joints that are devoid of synovial space. Treatment failures are most frequently the result of failure to enter the joint space. Little or no benefit follows injection into surrounding tissue. If failures occur when injections into the synovial spaces are certain, as determined by aspiration of fluid, repeated injections are usually futile.

If a local anesthetic is used prior to injection of methylprednisolone acetate injectable suspension, USP, the anesthetic package insert should be read carefully and all the precautions observed.

2. Bursitis

The area around the injection site is prepared in a sterile way and a wheal at the site made with 1 percent procaine hydrochloride solution. A 20 to 24 gauge needle attached to a dry syringe is inserted into the bursa and the fluid aspirated. The needle is left in place and the aspirating syringe changed for a small syringe containing the desired dose. After injection, the needle is withdrawn and a small dressing applied.

3. Miscellaneous: Ganglion, Tendinitis, Epicondylitis

In the treatment of conditions such as tendinitis or tenosynovitis, care should be taken, following application of a suitable antiseptic to the overlying skin, to inject the suspension into the tendon sheath rather than into the substance of the tendon. The tendon may be readily palpated when placed on a stretch. When treating conditions such as epicondylitis, the area of greatest tenderness should be outlined carefully and the suspension infiltrated into the area. For ganglia of the tendon sheaths, the suspension is injected directly into the cyst. In many cases, a single injection causes a marked decrease in the size of the cystic tumor and may effect disappearance. The usual sterile precautions should be observed, of course, with each injection.

The dose in the treatment of the various conditions of the tendinous or bursal structures listed above varies with the condition being treated and ranges from 4 to 30 mg. In recurrent or chronic conditions, repeated injections may be necessary.

4. Injections for Local Effect in Dermatologic Conditions

Following cleansing with an appropriate antiseptic such as 70% alcohol, 20 to 60 mg of the suspension is injected into the lesion. It may be necessary to distribute doses ranging from 20 to 40 mg by repeated local injections in the case of large lesions. Care should be taken to avoid injection of sufficient material to cause blanching since this may be followed by a small slough. One to four injections are usually employed, the intervals between injections varying with the type of lesion being treated and the duration of improvement produced by the initial injection.

When multidose vials are used, special care to prevent contamination of the contents is essential. (See WARNINGS)

B. Administration for Systemic Effect

The intramuscular dosage will vary with the condition being treated. When employed as a temporary substitute for oral therapy, a single injection during each 24-hour period of a dose of the suspension equal to the total daily oral dose of methylprednisolone tablets, USP is usually sufficient. When a prolonged effect is desired, the weekly dose may be calculated by multiplying the daily oral dose by 7 and given as a single intramuscular injection.

In pediatric patients, the initial dose of methylprednisolone may vary depending upon the specific disease entity being treated. The range of initial doses is 0.11 to 1.6 mg/kg/day. Dosage must be individualized according to the severity of the disease and response of the patient.

In patients with the adrenogenital syndrome, a single intramuscular injection of 40 mg every two weeks may be adequate. For maintenance of patients with rheumatoid arthritis, the weekly intramuscular dose will vary from 40 to 120 mg. The usual dosage for patients with dermatologic lesions benefited by systemic corticoid therapy is 40 to 120 mg of methylprednisolone acetate administered intramuscularly at weekly intervals for one to four weeks. In acute severe dermatitis due to poison ivy, relief may result within 8 to 12 hours following intramuscular administration of a single dose of 80 to 120 mg. In chronic contact dermatitis repeated injections at 5 to 10 day intervals may be necessary. In seborrheic dermatitis, a weekly dose of 80 mg may be adequate to control the condition.

Following intramuscular administration of 80 to 120 mg to asthmatic patients, relief may result within 6 to 48 hours and persist for several days to two weeks. Similarly in patients with allergic rhinitis (hay fever) an intramuscular dose of 80 to 120 mg may be followed by relief of coryzal symptoms within six hours persisting for several days to three weeks.

If signs of stress are associated with the condition being treated, the dosage of the suspension should be increased. If a rapid hormonal effect of maximum intensity is required, the intravenous administration of highly soluble methylprednisolone sodium succinate is indicated.

In treatment of acute exacerbations of multiple sclerosis daily doses of 160 mg of methylprednisolone for a week followed by 64 mg every other day for 1 month have been shown to be effective.

For the purpose of comparison, the following is the equivalent milligram dose of the various glucocorticoids:

Cortisone, 25 | Triamcinolone, 4
Hydrocortisone, 20 | Paramethasone, 2
Prednisolone, 5 | Netamethasone, 0.75
Prednisone, 5 | Dexamethasone, 0.75
Methylprednisolone, 4

Those dose relationships apply only to oral or intravenous administration of these compounds. When these substances or their derivatives are injected intramuscularly or into joint spaces, their relative properties may be greatly altered.

HOW SUPPLIED

Methylprednisolone acetate injectable suspension, USP is available in the following strengths and package sizes:

40 mg per mL
NDC 0703-0043-01 | 5 mL multidose vials, packaged individually
NDC 0703-0045-01 | 10 mL multidose vials, packaged individually
80 mg per mL
NDC 0703-0063-01 | 5 mL multidose vials, packaged individually

STORAGE AND HANDLING

Store at controlled room temperature 20°-25°C (68°-77°F) [see USP].

Rx only

Issued: May 2009

Manufactured by:
Teva Parenteral Medicines, Inc.
Irvine, CA 92618

Active ingredient

Povidone-Iodine USP 10% w/w (equivalent to 1.0% titratable iodine)

Purpose

Antiseptic

Uses

- Healthcare antiseptic for preparation of the skin prior to surgery
- First Aid antiseptic to help prevent the risk of skin infection in minor cut, scrapes and burns.

Warnings

For external use only
Do not use

- in the eyes
- on individuals who are allergic or sensitive to iodine
- over large areas of the body
- as a first aid antiseptic longer than one week unless directed by a doctor

Discontinue use if irritation and redness develop. If condition persist for more than 72 hours consult a doctor.
Consult a doctor in case of

- Deep or puncture wounds
- animal bites
- serious burns.

Stop and use and ask a doctor if

the condition persists or gets worse.

Keep out of reach of children.

If swallowed, get medical help or contact a Poison Control Center right away.

Directions

For the preparation of the skin prior to surgery

- clean the treatment area
- Remove swab by stick
- apply to the operative site prior to surgery

For use as a first aid antiseptic

- clean the treatment area
- apply a small amount of this product on the treatment area 1-3 times daily
- may be covered with a sterile bandage
- if bandaged, let dry first

Other information

- Store at room temperature
- Avoid excessive heat

Inactive ingredients

Purified Water, Sodium Hydroxide

Questions?

Professional Disposables International, Inc.
Orangeburg, NY 10962-1376
USA - 1-800-999-6423
www.pdipdi.com Made in USA

PRINCIPAL DISPLAY PANEL – SWAB LABEL

PDI®

REORDER NO. C124

NDC 10819-3883-3

Povidone-Iodine Prep Pad

Antiseptic/Germicide Large

For Professional and Hospital Use

Professional Disposables International, Inc.

Orangeburg, NY 10962-1376 • USA • 1-800-999-6423

www.pdipdi.com Made in USA

1 Prep Pad [1.7 x 3.5 in (4.4 x 8.8 cm)]

PRINCIPAL DISPLAY PANEL - 5ML VIAL LABEL

NDC 0703-0043-01

Rx only

METHYLPREDnisolone
ACETATE Injectable Suspension, USP

40 mg/mL

For IM, intrasynovial and soft
tissue injection only.

5 mL Multi Dose Vial

Sterile

TEVA

PRINCIPAL DISPLAY PANEL - 10ML VIAL LABEL

10 mL (50 mg) NDC 0409-1560-10

SINGLE-DOSE VIAL- PRESERVATIVE FREE M-612

Marcaine® 0.5%

bupivacaine HCl injection, USP

for NERVE BLOCK. CAUDAL and

EPIDURAL ANESTHESIA

NOT FOR SPINAL ANESTHESIA

Rx only Hospira

PACKAGE LABEL

PRINCIPAL DISPLAY PANEL - KIT CARTON

NDC 76420-0520-01 RX-Only

Physicians EZ Use
M-pred
Injection Kit

Kit Contains:
1 Marcaine® 0.5% Single Dose Vial (10mL)*
1 Methylprednisone Acetate Injection Suspension,
USP 40mg/mL Multiple Dose Vial (5mL)*
1 Povidone-Iodine Prep Pad

1 Pair Sterile Latex Gloves - Size 7*
1 CSR Wrap

1 Dose

Relabeled By:

Proficient Rx LP Thousand Oaks, CA 91320